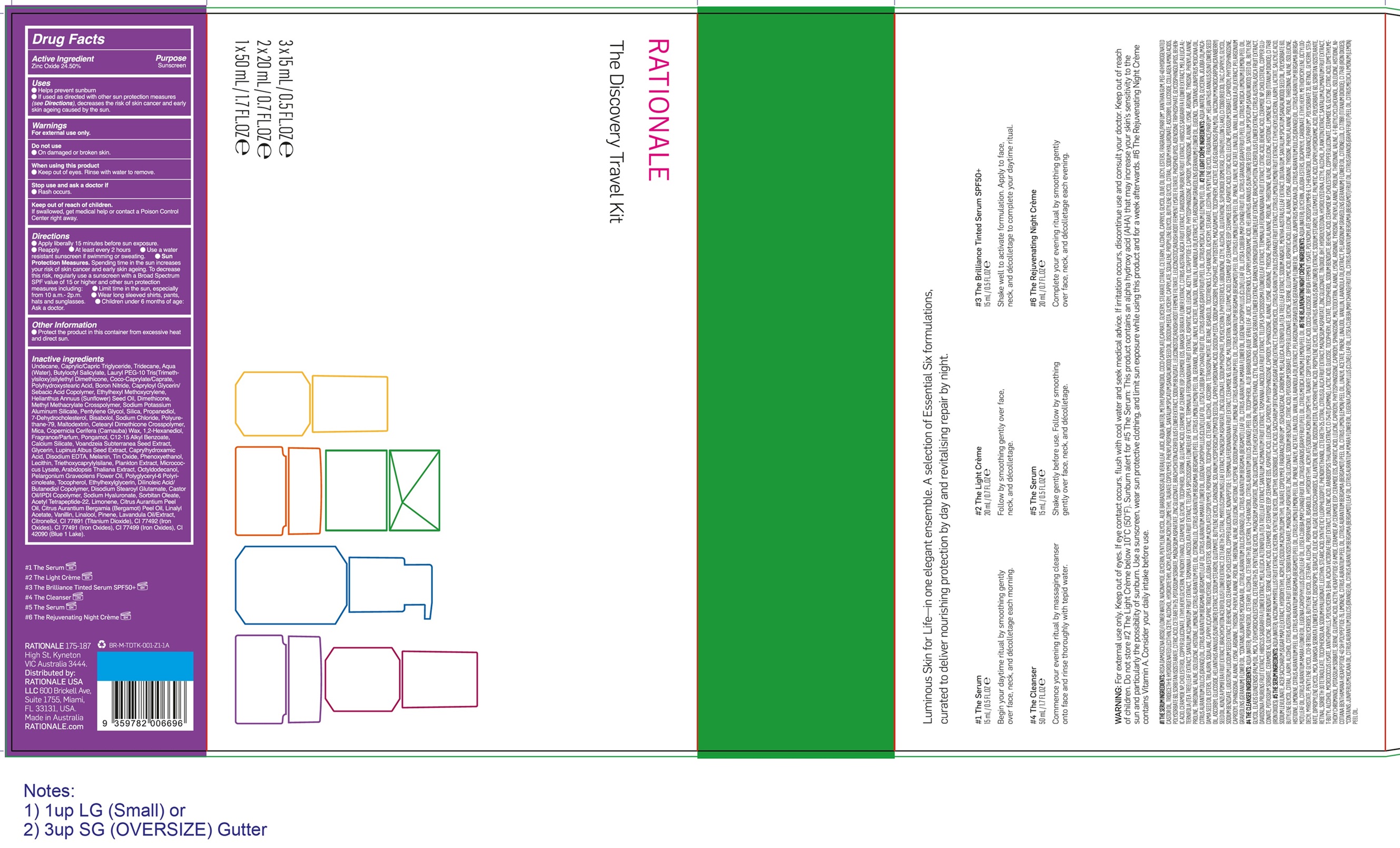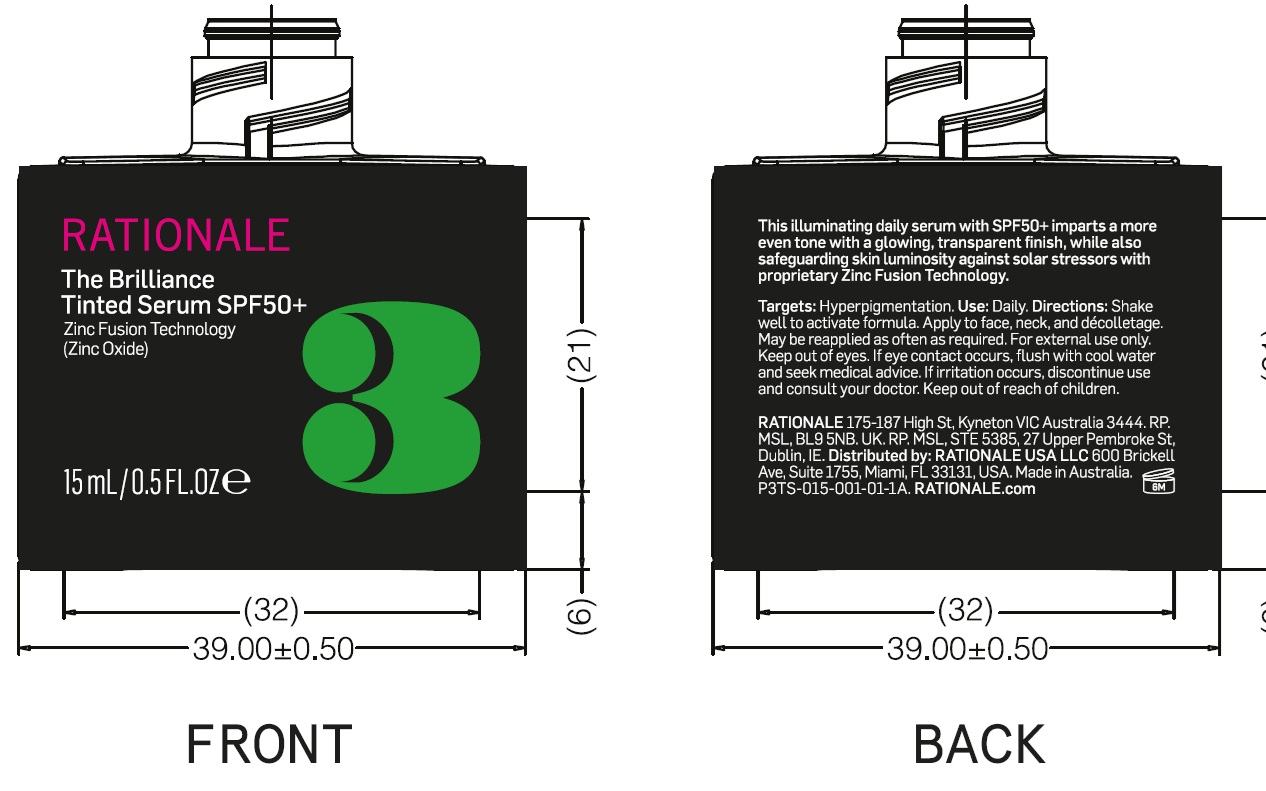 DRUG LABEL: Rationale The Discovery Travel Kit
NDC: 83108-210 | Form: KIT | Route: TOPICAL
Manufacturer: RATIONALE GROUP PTY LTD
Category: otc | Type: HUMAN OTC DRUG LABEL
Date: 20260225

ACTIVE INGREDIENTS: ZINC OXIDE 245 mg/1 mL
INACTIVE INGREDIENTS: UNDECANE; CAPRYLIC/CAPRIC TRIGLYCERIDE; TRIDECANE; WATER; BUTYLOCTYL SALICYLATE; COCOYL CAPRYLOCAPRATE; BORON NITRIDE; ETHYLHEXYL METHOXYCRYLENE; HELIANTHUS ANNUUS (SUNFLOWER) SEED OIL; DIMETHICONE; SODIUM POTASSIUM ALUMINUM SILICATE; PENTYLENE GLYCOL; SILICA; PROPANEDIOL; 7-DEHYDROCHOLESTEROL; BISABOLOL; SODIUM CHLORIDE; MALTODEXTRIN; MICA; COPERNICIA CERIFERA (CARNAUBA) WAX; PONGAMOL; C12-15 ALKYL BENZOATE; CALCIUM SILICATE; BAMBARA GROUNDNUT; GLYCERIN; LUPINUS ALBUS SEED; CAPRYLHYDROXAMIC ACID; EDETATE DISODIUM; TIN OXIDE; PHENOXYETHANOL; TRIETHOXYCAPRYLYLSILANE; ARABIDOPSIS THALIANA WHOLE; OCTYLDODECANOL; PELARGONIUM GRAVEOLENS FLOWER OIL; TOCOPHEROL; ETHYLHEXYLGLYCERIN; DILINOLEIC ACID/BUTANEDIOL COPOLYMER; DISODIUM STEAROYL GLUTAMATE; CASTOR OIL/IPDI COPOLYMER; HYALURONATE SODIUM; SORBITAN OLEATE; LIMONENE, (+)-; CITRUS AURANTIUM PEEL OIL; BERGAMOT OIL; LINALYL ACETATE; VANILLIN; LINALOOL; PINENE; .BETA.-CITRONELLOL, (R)-; TITANIUM DIOXIDE; FERRIC OXIDE YELLOW; FERRIC OXIDE RED; FERROSOFERRIC OXIDE; FD&C BLUE NO. 1

Rationale The Brilliance Tinted Serum SPF 50

Active Ingredient

Zinc Oxide 24.50%

Purpose

Sunscreen

Uses

- Helps prevent sunburn
- If used as directed with other other sun protection measures (see Directions), decreases the risk of skin cancer and early skin ageing caused by the sun

Warnings

For external use only.

Do not use

- On damaged or broken skin.

When using this product

- Keep out of eyes. Rinse with water to remove.

Stop use and ask a doctor if

- Rash occurs.

Keep out of reach of children.

If swallowed, get medical help or contact a Poison Control Center right away

Directions

- Apply liberally 15 minutes before sun exposure.
- Reapply
- At least every 2 hours
- Use a water resistant sunscreen if swimming or sweating.
- Sun Protection Measures. Spending time in the sun increases your risk of skin cancer and early skin ageing. To decrease this risk, regularly use a sunscreen with a Broad Spectrum SPF value of 15 or higher and other sun protection measures including:
- Limit time in the sun, especially from 10 a.m.- 2 p.m.
- Wear long sleeved shirts, pants, hats and sunglasses.
- Children under 6 months of age:Ask a doctor

Other information

- Protect the product in this container from exceesive heat and direct sun.

Inactive ingredients

Undecane, Caprylic/Capric Triglyceride, Tridecane, Aqua (Water), Butyloctyl Salicylate, Lauryl PEG-IO Tris(Trimethylsi- loxy)silylethyl Dimethicone, Coco-Caprylate/• Caprate, Polyhydroxystearic Acid, Boron Nitride, Capryloyl Glycerin/Sebacic Acid Copolymer, Ethylhexyl Methoxycrylene, Helianthus Annuus (Sunflower) Seed Oil, Dimethicone, Methyl Methacrylate Crosspolymer, Sodium Potassium Aluminum Silicate, Pentylene Glycol, Silica, Propanediol, 7-Dehydrocholesterol, Bisabolol, Sodium Chloride, Polyurethane-79, Maltodextrin, Cetearyl Dimethicone Crosspolymer, Mica, Copernicia Cerifera (Carnauba) Wax, I ,2•HexanedioI, Fragrance/Parfum, Pongamol, C12-15 Alkyl Benzoate, Calcium Silicate, Voandzeia Subterranea Seed Extract, Glycerin, Lupinus Albus Seed Extract, Caprylhydroxamic Acid Disodium EDTA, Melanin, Tin Oxide,Phenoxyethanol, Lecithin, Triethoxycapry- lylsilane, Plankton Extract, Micrococcus Lysate, Arabidopsis Thaliana Extract, Octyldodecanol, Pelargonium Graveolens Flower Oil, PolyglyceryI•6 Polyricinoleate, Tocopherol, Ethylhexylglycerin, Dilinoleic Acid/ButanedioI Copolymer, Disodium Stearoyl Glutamate, Castor Oil/IPDI Copolymer, Sodium Hyaluronate, Sorbitan Oleate, Acetyl Tetrapeptide-22, Limonene, Citrus Aurantium Peel Oil, Citrus Aurantium Bergamia (Bergamot) Peel Oil, Linalyl Acetate, Vanillin, Linalool, Pinene, Lavandula OiVExtract, Citronellol, CI 77891 (Titanium Dioxide), CI 77492 (Iron Oxides), Cl 77491 (Iron Oxides), Cl 77499 (Iron Oxides), Cl 42090 (Blue 1 Lake).